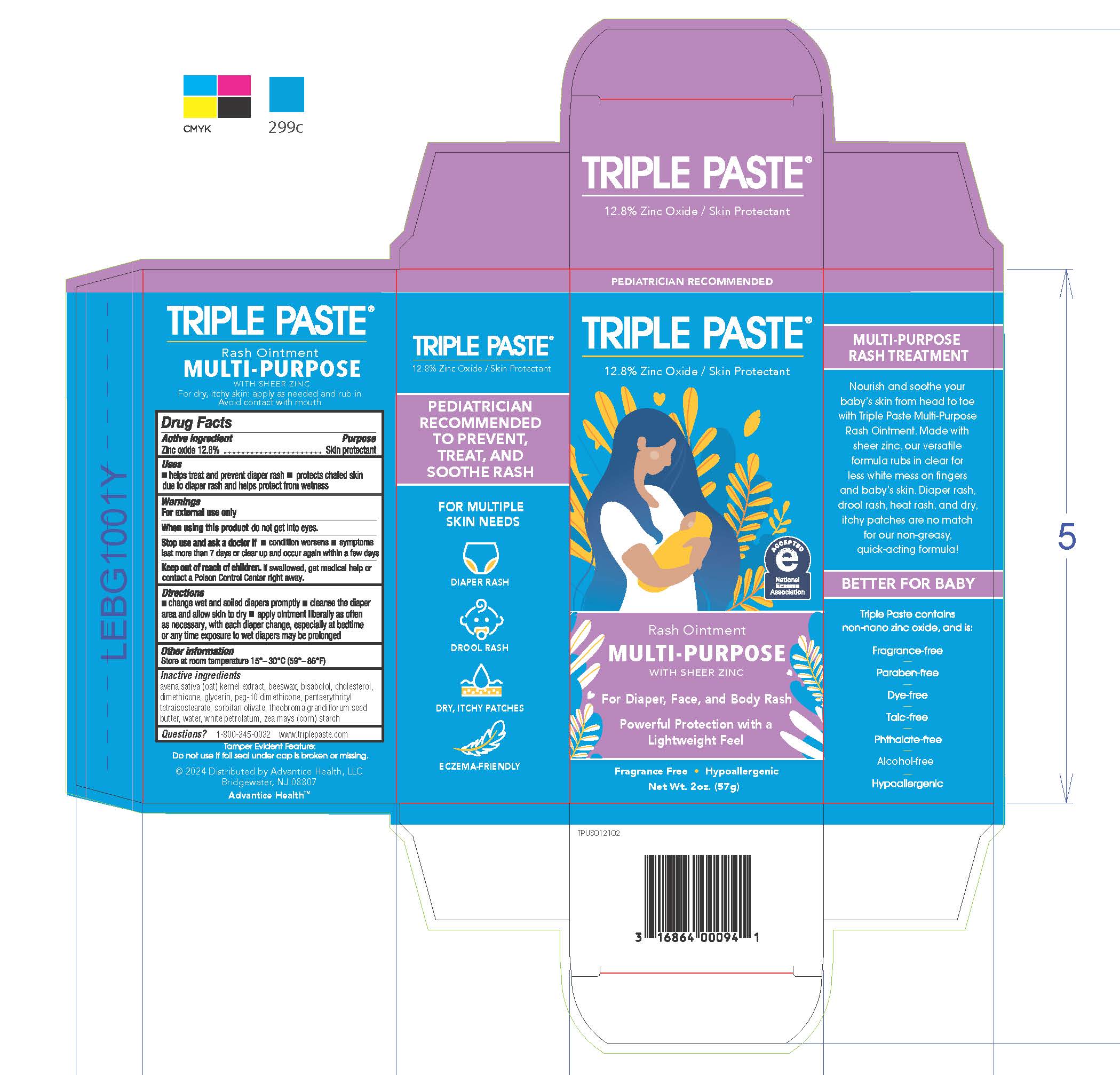 DRUG LABEL: multipurpose
NDC: 16864-041 | Form: OINTMENT
Manufacturer: Advantice Health, LLC
Category: otc | Type: HUMAN OTC DRUG LABEL
Date: 20241212

ACTIVE INGREDIENTS: ZINC OXIDE 12.8 g/100 g
INACTIVE INGREDIENTS: STARCH, CORN; PEG-10 DIMETHICONE (200 CST); LEVOMENOL; PENTAERYTHRITYL TETRAISOSTEARATE; DIMETHICONE, UNSPECIFIED; CHOLESTEROL; OAT; SORBITAN OLIVATE; WATER; GLYCERIN; WHITE PETROLATUM; YELLOW WAX

Triple Paste MultiPurpose Rash Ointment

ACTIVE INGREDIENT

Zinc Oxide 12.8%

PURPOSE

Skin Protectant

WARNINGS

For external use only.

WHEN USING

do not get into eyes

STOP USE

■ condition worsens ■ symptoms last more than 7 days or clear up and occur again within a few days

KEEP OUT OF REACH OF CHILDREN

If swallowed, get medical help or contact a Poison Control Center right away.

DOSAGE AND ADMINISTRATION

■ change wet and soiled diapers promptly ■ cleanse the diaper area and allow skin to dry ■ apply ointment liberally as often
as necessary, with each diaper change, especially at bedtime or any time exposure to wet diapers may be prolonged

STORAGE AND HANDLING

Store at room temperature 15-30C (59-86F)

INACTIVE INGREDIENT

avena sativa (oat) kernel extract, beeswax, bisabolol, cholesterol, dimethicone, glycerin, peg-10 dimethicone, pentaerythrityl tetraisostearate, sorbitan olivate, theobroma grandiflorum seed butter, water, white petrolatum, zea mays (corn) starch

QUESTIONS

1-800-345-0032 www.triplepaste.com

2024 Distributed by Advantice Health, LLC
Bridgewater, NJ 08807

INDICATIONS AND USAGE

■ helps treat and prevent diaper rash ■ protects chafed skin due to diaper rash and helps protect from wetness

PACKAGE LABEL

Triple Paste

12.8% zinc oxide / skin protectant

Rash Ointment

Multi-Purpose with Sheer Zinc

for diaper, face and body rash

Powerful portection with a lightweight feel

Fragrance free - Hypoallergenic

Net Wt. 2oz (57g)